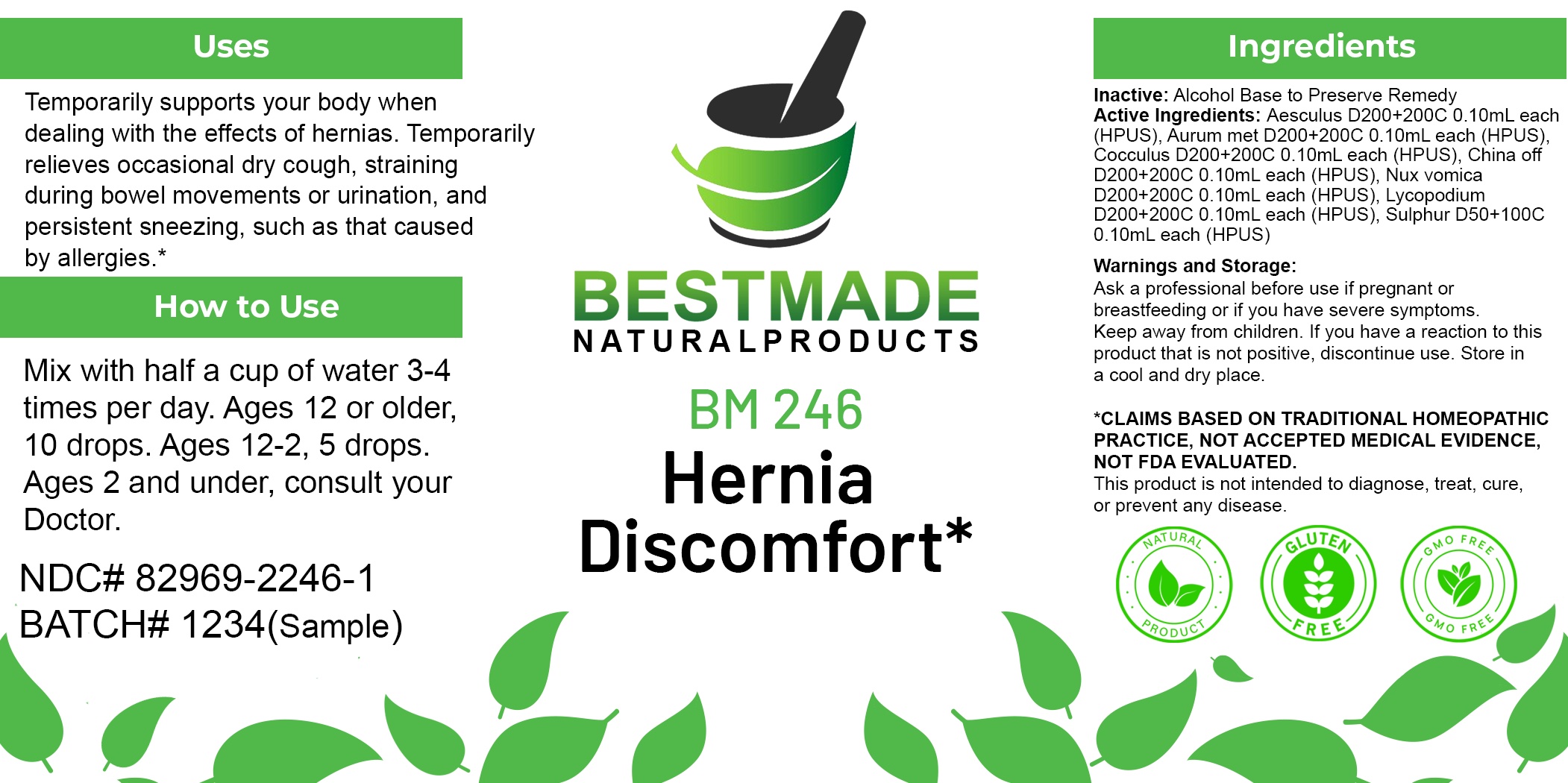 DRUG LABEL: Bestmade Natural Products BM246
NDC: 82969-2246 | Form: LIQUID
Manufacturer: Bestmade Natural Products
Category: homeopathic | Type: HUMAN OTC DRUG LABEL
Date: 20250305

ACTIVE INGREDIENTS: CINCHONA OFFICINALIS BARK 30 [hp_C]/30 [hp_C]; SULFUR 30 [hp_C]/30 [hp_C]; STRYCHNOS NUX-VOMICA SEED 30 [hp_C]/30 [hp_C]; LYCOPODIUM CLAVATUM SPORE 30 [hp_C]/30 [hp_C]; GOLD 30 [hp_C]/30 [hp_C]; ANAMIRTA COCCULUS SEED 30 [hp_C]/30 [hp_C]; HORSE CHESTNUT 30 [hp_C]/30 [hp_C]
INACTIVE INGREDIENTS: ALCOHOL 30 [hp_C]/30 [hp_C]

BM246

DOSAGE AND ADMINISTRATION

How to Use

Mix with half a cup of water 3-4 times per day. Ages 12 or older, 10 drops. Ages 12-2, 5 drops. Ages 2 and under, consult your Doctor.

Inactive:

Alcohol Base to Preserve Product

ACTIVE INGREDIENTS

Aesculus D200+200C 0.10mL each (HPUS), Aurum met D200+200C 0.10mL each (HPUS), Cocculus D200+200C 0.10mL each (HPUS), China off D200+200C 0.10mL each (HPUS), Nux vomica D200+200C 0.10mL each (HPUS), Lycopodium D200+200C 0.10mL each (HPUS), Sulphur D50+100C 0.10mL each (HPUS)

KEEP OUT OF REACH OF CHILDREN

Warnings and Storage:

Ask a professional before use if pregnant or breastfeeding or if you have severe symptoms.

Keep away from children. If you have a reaction to this product that is not positive, discontinue use. Store in a cool and dry place

*CLAIMS BASED ON TRADITIONAL HOMEOPATHIC PRACTICE, NOT ACCEPTED MEDICAL EVIDENCE NOT FDA EVALUATED.
This product is not intended to diagnose, treat, cure, or prevent any disease.

Warnings and Storage:

Ask a professional before use if pregnant or breastfeeding or if you have severe symptoms.

Keep away from children. If you have a reaction to this product that is not positive, discontinue use. Store in a cool and dry place

*CLAIMS BASED ON TRADITIONAL HOMEOPATHIC PRACTICE, NOT ACCEPTED MEDICAL EVIDENCE NOT FDA EVALUATED.
This product is not intended to diagnose, treat, cure, or prevent any disease.

Uses
Temporarily supports your body when dealing with the effects of hernias. Temporarily relieves occasional dry cough, straining
during bowel movements or urination, and persistent sneezing, such as that caused by allergies.*

Uses
Temporarily supports your body when dealing with the effects of hernias. Temporarily relieves occasional dry cough, straining
during bowel movements or urination, and persistent sneezing, such as that caused by allergies.*

Entire package label